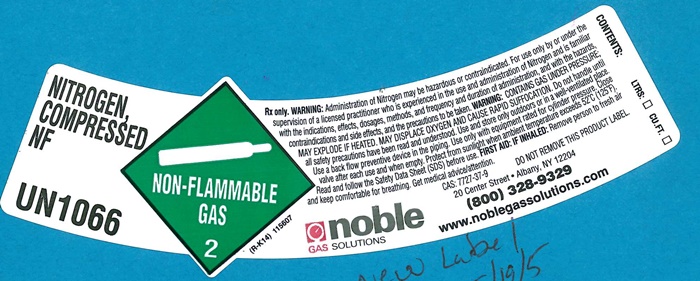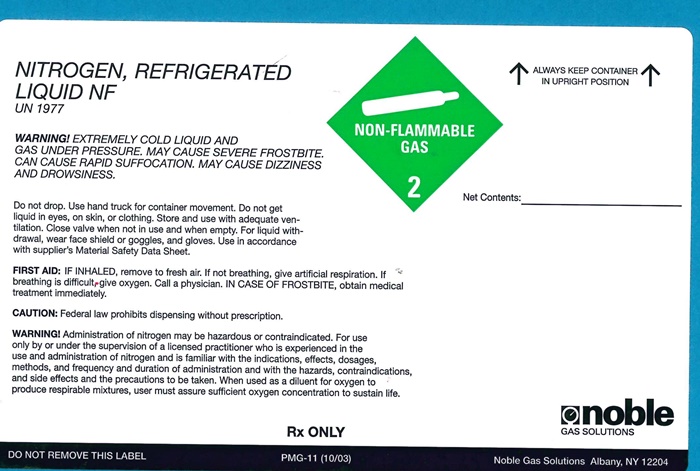 DRUG LABEL: NITROGEN
NDC: 17819-1066 | Form: GAS
Manufacturer: Noble Gas Solutions, Inc.
Category: prescription | Type: HUMAN PRESCRIPTION DRUG LABEL
Date: 20241006

ACTIVE INGREDIENTS: NITROGEN 99 L/100 L

Nitrogen

NITROGEN COMPRESSED NF product label

NITROGEN COMPRESSED NF

UN1066

NON-FLAMMABLE GAS 2

(R-K14) 115607

Rx only. WARNING: Administration of Nitrogen may be hazardous or contraindicated. For use only by or under the supervision of a licensed practitioner who is experienced in the use and administration of Nitrogen and is familiar with the indications, effects, dosages, methods, and frequency and duration of administration, and with the hazards, contraindications and side effects, and the precautions to be taken. WARNING: CONTAINS GAS UNDER PRESSURE; MAY EXPLODE IF HEATED. MAY DISPLACE OXYGEN AND CAUSE RAPID SUFFOCATION. Do not handle until all safety precautions have been read and understood. Use and store only outdoors or in a well-ventilated place. Use a back flow preventive device in the piping. Use only with equipment rated for cylinder pressure. Close valve after each use and when empty. Protect from sunlight when ambient temperature exceeds 52°C(125°F). Read and follow the safety data Sheet (SDS) before use. FIRST AID: IF INHALED: Remove person to fresh air and kkep comfortable for breathing. Get medical advice/attention.

CAS:7727-37-9 DO NOT REMOVE THIS PRODUCT LABEL

NOBLE GAS SOLUTIONS
20 Center Street • Albany, NY 12204
(800) 328-9329

www.noblegassolutions.com

CONTENTS: LTRS CU.FT.

NITROGEN, REFRIDERATED LIQUID NF product label

NITROGEN, REFRIGERATED LIQUID NF

UN 1977

NON-FLAMMABLE GAS 2

↑ALWAYS KEEP CONTAINER IN UPRIGHT POSITION↑

Net Contents: _______

WARNING! EXTREMELY COLD LIQUID AND GAS UNDER PRESSURE. MAY CAUSE SEVERE FROSTBITE. CAN CAUSE RAPID SUFFOCATION. MAY CAUSE DIZZINESS AND DROWSINESS.

Do not drop. Use a hand truck for container movement. Do not get liquid in eyes, on skin, or clothing. Store and use adequate ventilation. Close valve when not in use and when empty. For liquid withdrawal, wear face shield or goggles, and gloves. Use in accordance with supplier's Marerial Safety Data Sheet.

FIRST AID: If Inhaled, remove to fresh air. If not breathing, give artificial Respiration. If breathing is difficult, give oxygen. Call a physician. IN CASE OF FROSTBITE, obtain treatment immediately.

CAUTION: Federal law prohibits dispensing without prescription.

WARNING! Administration of Nitrogen may be hazardous or contraindicated. For use only by or under the supervision of a licensed practitioner who is experienced in the use and administration of Nitrogen and is familiar with the indications, effects, dosages, methods, and frequency and duration of administration, and with the hazards, contraindications and side effects, and the precautions to be taken. When used as a diluent for oxygen to produce respirable mixtures, user must assure sufficient oxygen concentration to sustain life.

Rx ONLY

DO NOT REMOVE THIS LABEL PMG-11 (10/03)

NOBLE GAS SOLUTIONS
Albany, NY 12204